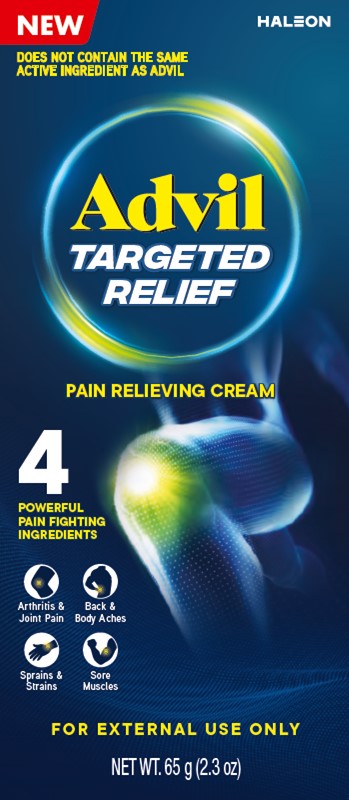 DRUG LABEL: Advil Targeted Relief
NDC: 0573-6555 | Form: CREAM
Manufacturer: Haleon US Holdings LLC
Category: otc | Type: HUMAN OTC DRUG LABEL
Date: 20240208

ACTIVE INGREDIENTS: CAMPHOR (NATURAL) 31 mg/1 g; CAPSAICIN 0.25 mg/1 g; MENTHOL, UNSPECIFIED FORM 100 mg/1 g; METHYL SALICYLATE 150 mg/1 g
INACTIVE INGREDIENTS: CARBOMER HOMOPOLYMER, UNSPECIFIED TYPE; CETYL ALCOHOL; CETYL ESTERS WAX; ISOCETYL STEARATE; CARNAUBA WAX; OLETH-3 PHOSPHATE; WATER; SODIUM HYDROXIDE; STEARIC ACID

Drug Facts

Active ingredients

Camphor 3.1%

Capsaicin 0.025%

Menthol 10%

Methyl salicylate 15%

Purposes

Topical analgesic

Topical analgesic

Topical analgesic

Topical analgesic

Uses

- Temporarily relieves minor aches and pains of muscles and joints associated with:

- arthritis
- strains
- simple backache
- bruises
- sprains

Warnings

For external use only

- avoid contact with eyes. If eye contact occurs, rinse thoroughly with water.

Do not use

- on wounds or damaged skin
- with a heating pad
- if you are allergic to any ingredients in this product

Ask a doctor before use if you have

- redness over the affected area

When using this product

- do not bandage tightly

Stop use and ask a doctor if

- condition worsens or if symptoms last for more than 7 days
- symptoms clear up and occur again within a few days
- rash, itching or skin irritation develops

Directions

- use only as directed
- adults and children 12 years and older: apply to affected area not more than 3 to 4 times daily
- children under 12 years of age: consult your doctor
- wash hands after applying

Other information

- store between 20-25°C (68-77°F)

Inactive ingredients

carbomer homopolymer, cetyl alcohol, cetyl esters wax, emulsifying wax, oleth-3-phosphate, purified water, sodium hydroxide, stearic acid

Questions or comments?

call toll-free 1-800-88-ADVIL

Additional information

DEEP PENETRATING RELIEF

BACK & BODY ACHES

ARTHRITIS & JOINT PAIN

SPRAINS & STRAINS

SORE MUSCLES

STARTS WORKING ON CONTACT

FOR UP TO 8 HOURS OF POWERFUL RELIEF

UP TO 8 HRS

HOW TO USE

Clean and dry affected area

Remove cap

Gently squeeze to dispense cream

Massage cream into skin

Starts to soothe on contact

Do Not Use if tube seal under cap is broken or missing.

Distributed by: Haleon, Warren, NJ 07059

©2023 Haleon group of companies or its licensor.

Trademarks are owned by or licensed to the Haleon group of companies.

For most recent product information, visit www.Advil.com

Made in Canada

PRINCIPAL DISPLAY PANEL

NEW HALEON
DOES NOT CONTAIN THE SAME ACTIVE INGREDIENT AS ADVIL
Advil

TARGETED

RELIEF

PAIN RELIEVING CREAM

4 POWERFUL PAIN FIGHTING INGREDIENTS

Arthritis & Joint Pain

Sprains & Strains

Back & Body aches

Sore Muscles

FOR EXTERNAL USE ONLY

NET WT. 65 g (2.3 oz)

206239 Front